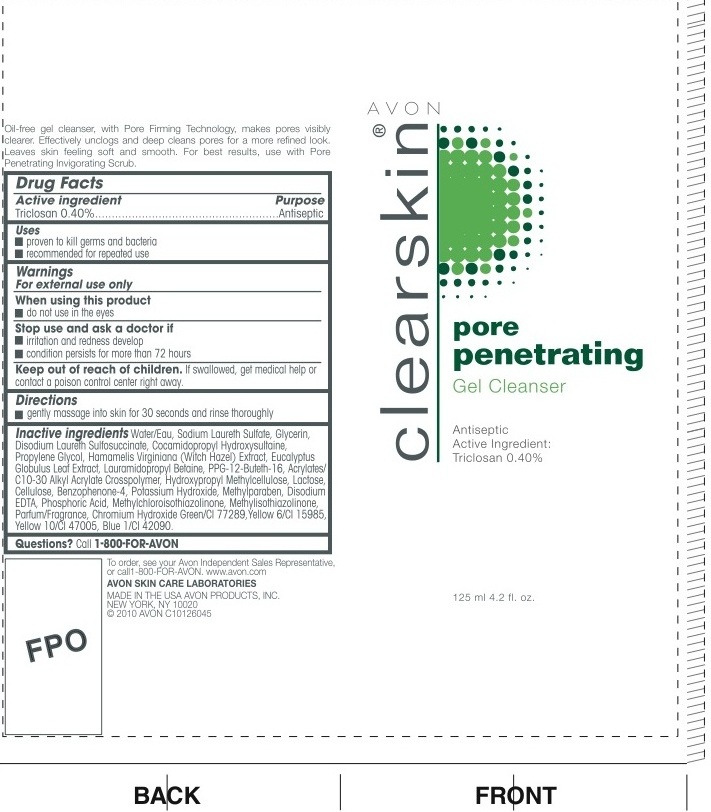 DRUG LABEL: Clearskin
NDC: 10096-0199 | Form: GEL
Manufacturer: Avon Products, Inc.
Category: otc | Type: HUMAN OTC DRUG LABEL
Date: 20100602

ACTIVE INGREDIENTS: TRICLOSAN 0.5 mL/125 mL
INACTIVE INGREDIENTS: WATER; SODIUM LAURETH SULFATE; GLYCERIN; DISODIUM LAURETH SULFOSUCCINATE; PROPYLENE GLYCOL; LAURAMIDOPROPYL BETAINE; LACTOSE; POTASSIUM HYDROXIDE; METHYLPARABEN; PHOSPHORIC ACID; METHYLCHLOROISOTHIAZOLINONE; METHYLISOTHIAZOLINONE

Drug Facts

Active ingredient Purpose

Triclosan 0.40%..................................Antiseptic

Uses

- proven to kill germs and bacteria
- recommended for repeated use

Warnings
For external use only

When using this product

- do not use in the eyes

Stop use and ask a doctor if

- irritation and redness develop
- condition persists for more than 72 hours

Keep out of reach of children. If swallowed, get medical help or contact a poison control center right away.

Directions

- gently massage into skin for 30 seconds and rinse thoroughly

Inactive Ingredients
WATER/EAU
SODIUM LAURETH SULFATE
GLYCERIN
DISODIUM LAURETH SULFOSUCCINATE
COCAMIDOPROPYL HYDROXYSULTAINE
PROPYLENE GLYCOL
HAMAMELIS VIRGINIANA (WITCH HAZEL) EXTRACT
EUCALYPTUS GLOBULUS LEAF EXTRACT
LAURAMIDOPROPYL BETAINE
PPG-12-BUTETH-16
ACRYLATES/C10-30 ALKYL ACRYLATE CROSSPOLYMER
HYDROXYPROPYL METHYLCELLULOSE
LACTOSE
CELLULOSE
BENZOPHENONE-4
POTASSIUM HYDROXIDE
METHYLPARABEN
DISODIUM EDTA
PHOSPHORIC ACID
METHYLCHLOROISOTHIAZOLINONE
METHYLISOTHIAZOLINONE
PARFUM/FRAGRANCE
CHROMIUM HYDROXIDE GREEN/CI 77289
YELLOW 6/CI 15985
YELLOW 10/CI 47005
BLUE 1/CI 42090

Questions? Call 1-800-FOR-AVON